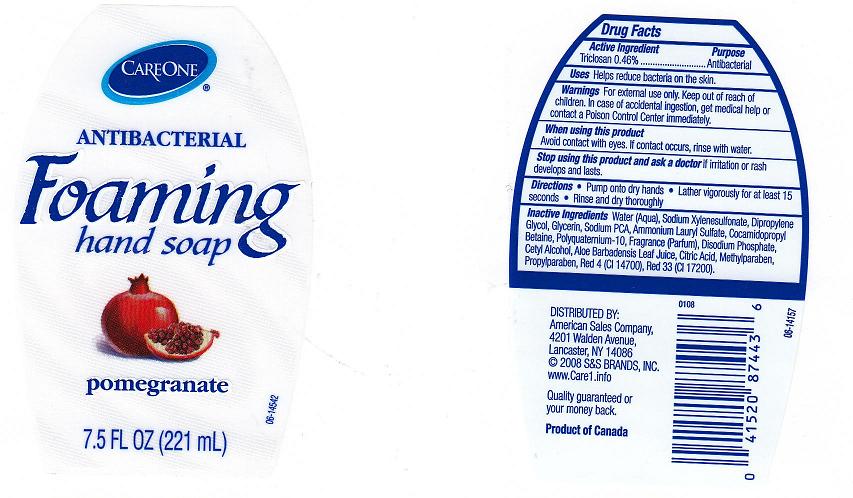 DRUG LABEL: ANTIBACTERIAL FOAMING
NDC: 63148-164 | Form: LIQUID
Manufacturer: Apollo Health and Beauty Care
Category: otc | Type: HUMAN OTC DRUG LABEL
Date: 20100706

ACTIVE INGREDIENTS: TRICLOSAN 0.4600 mL/100 mL

BACK LABEL - DRUG FACTS BOX

ACTIVE INGREDIENT

TRICLOSAN 0.46% (ANTIBACTERIAL)

USES AND DIRECTIONS

- USES: HELPS REDUCE BACTERIA ON THE SKIN.
- DIRECTIONS:PUMP ONTO DRY HANDS. LATHER VIGOROUSLY FOR AT LEAST 15 SECONDS. RINSE AND DRYTHOROUGHLY.

WARNINGS

- FOR EXTERNAL USE ONLY. KEEP OUT OF REACH OF CHILDREN. IN CASE OF ACCIDENTAL INGESTION, GET MEDICAL HELP OR CONTACT A POISON CONTROL CENTER IMMEDIATELY.

WHEN USING THIS PRODUCT

- AVOID CONTACT WITH EYES, IF CONTACT OCCURS, RINSE WITH WATER.

STOP USING THIS PRODUCT AND ASK A DOCTOR

- IF IRRITATION OR RASH DEVELOPS AND LASTS.

PACKAGE FRONT AND BACK LABELS

7.5OZ FRONT AND BACK LABELS: care8.jpg